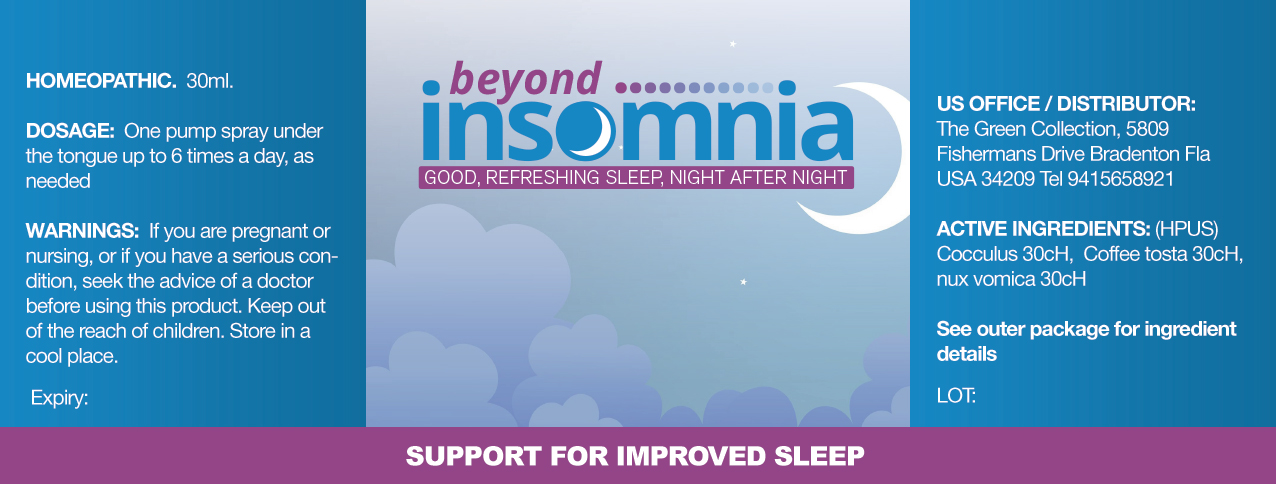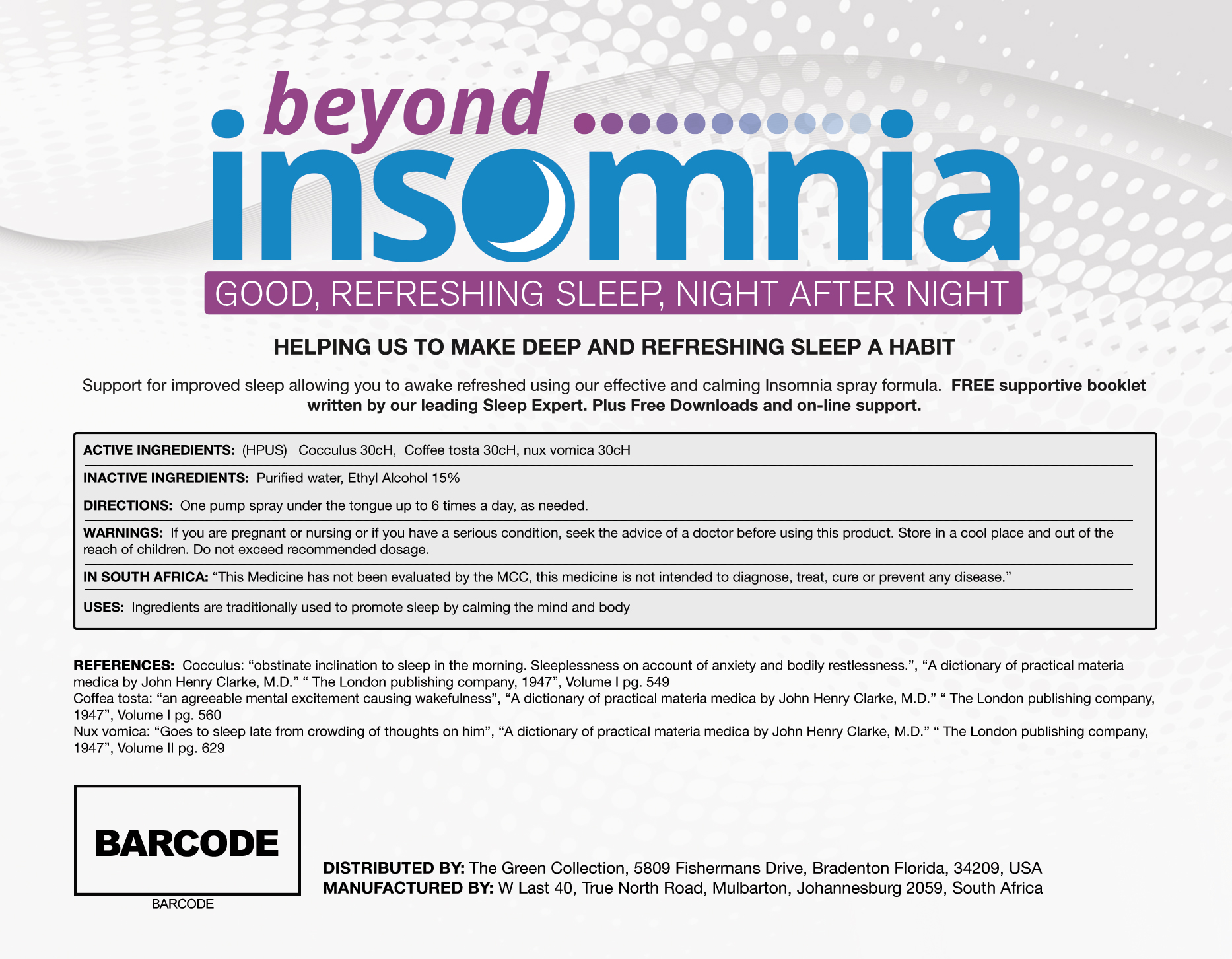 DRUG LABEL: beyond insomnia
NDC: 58214-456 | Form: SPRAY
Manufacturer: JMSP USA LLC
Category: homeopathic | Type: HUMAN OTC DRUG LABEL
Date: 20130417

ACTIVE INGREDIENTS: ANAMIRTA COCCULUS SEED 30 [hp_C]/30 mL; COFFEA ARABICA SEED, ROASTED 30 1/30 mL; STRYCHNOS NUX-VOMICA SEED 30 1/30 mL
INACTIVE INGREDIENTS: WATER 30 1/30 mL; ALCOHOL

Beyond Insomnia

Active Ingrdietns

Cocculus 30cH

Coffee tosta 30cH

nux vomica 30cH

Purpose

Promote sleep by calming the mind and body

Keep out of reach of children

Warnings

Not intended for pregnant or lactating women
Not to be taken by those with existing medical conditions, please consult your prior to use.

Inactive Ingredients:

Purified Water, Ethyl Alcohol 15%

Directions

One pump spray under the tongue up to 6 times a day, or as needed

Usage

Traditionally used to promote sleep by calming the mind and body